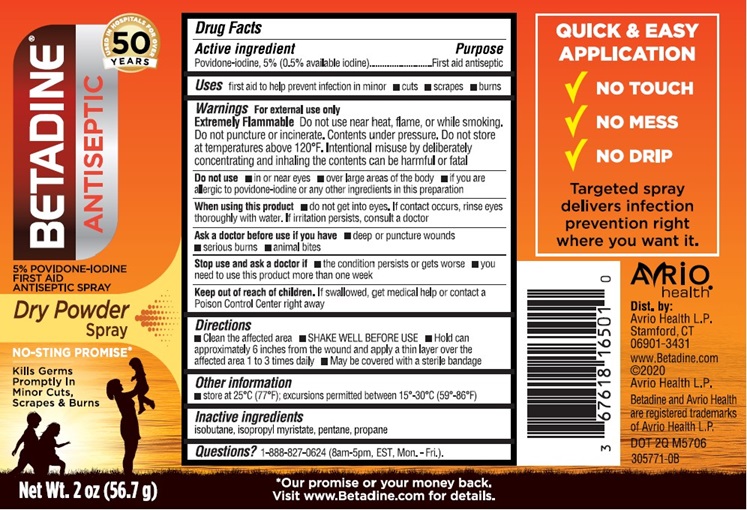 DRUG LABEL: Betadine Dry Powder
NDC: 67618-165 | Form: AEROSOL, SPRAY
Manufacturer: Atlantis Consumer Healthcare, Inc.
Category: otc | Type: HUMAN OTC DRUG LABEL
Date: 20241226

ACTIVE INGREDIENTS: POVIDONE-IODINE .05 mg/1 mL
INACTIVE INGREDIENTS: ISOBUTANE; ISOPROPYL MYRISTATE; PROPANE; METHOXYFLURANE

BETADINE® Dry Powder Spray
5%Povidone-iodine

Drug Facts

Active ingredient

Povidone-iodine,5% (0.5% available iodine).

Purpose

First aidantiseptic

Uses

First aidto help prevent infection in minor

- cuts
- scrapes
- burns

Warnings For external use only

Extremely Flammable Do not use near heat, flame or while smoking. Do notpuncture or incinerate. Contents under pressure. Do not store at temperaturesabove 120⁰F. Intentional misuse by deliberately concentrating andinhaling the contents can be harmful or fatal

Do not use

- in or near eyes
- over large areas of the body
- if you are allergic to povidone-iodine or any other ingredientsin this preparation

When using this product

- do not get into eyes. If contact occurs, rinse eyes thoroughlywith water. If irritation persists, consult a doctor.

Ask a doctor before use if you have

- deep or puncture wounds
- serious burns
- animal bites

Stop use and ask a doctor if

- the condition persists or gets worse
- you need to use this product for more than 1 week

Keep out of reachof children.
If swallowed, get medicalhelp or contact a Poison Control Center right away.

Directions

- Clean the affected area
- SHAKE WELL BEFORE USE
- Hold can approximately 6 inches from wound and apply a thinlayer over affected area 1 to 3 daily
- May be covered with a sterile bandage

Other information

- store at 25°C (77°F); excursions permitted between 15°-30°C(59°-86°F)

Inactive ingredients

Isobutane,isopropyl myristate, pentrane, propane

Dist. by: AvrioHealth L.P. Stamford, CT 06901-3431
305653-0A

PACKAGE LABEL

BetadineDry Powder Spray
NDC: 67618-165-01